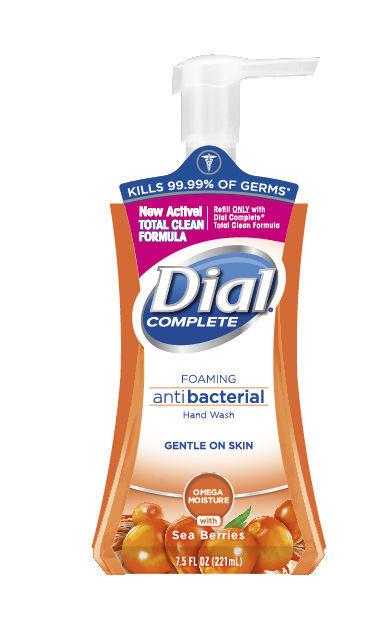 DRUG LABEL: Dial Foaming Hand Wash
NDC: 54340-247 | Form: SOLUTION
Manufacturer: The Dial Corporation, A Henkel Company
Category: otc | Type: HUMAN OTC DRUG LABEL
Date: 20151201

ACTIVE INGREDIENTS: BENZETHONIUM CHLORIDE 0.2 g/100 mL
INACTIVE INGREDIENTS: WATER

Dial Complete Omega Moisture Foaming Antibacterial Hand Wash

KILLS MORE GERMS

Than Ordinary Liquid Hand Soap

Others*

After washing with other ordinary hand soap.

Dial Complete*

After washing with Dial Complete Foaming Antibacterial Hand Wash

*Dramatization only: Number of organisms shown does not reflect actual number of bacteria.

Drug Facts

Active Ingredient

Benzethonium Chloride 0.20%

PURPOSE

Antibacterial

PURPOSE

Uses - For handwashing to decrease bacteria on the skin

WARNINGS

For external use only.

When using this product

- avoid contact with eyes. In case of eye contact, flush with water.

Stop use and ask a doctor if irritation or redness develops.

Keep out of reach of children. If swallowed, get medical help or contact a Poison Control Center right away.

Directions

- pump into DRY hands
- lather vigorously for at least 15 seconds
- rinse and dry thoroughly

INACTIVE INGREDIENT

Inactive Ingredients: Water, Glycerin, Lauramine Oxide, Fragrance, Sunflowerseedamidopropyl Ethyldimonium Ethosulfate and PEG-9, Cocamidopropyl Betaine, Hydroxypropyl Methylcellulose, Hippophae Rhamnoides Fruit Juice, Linoleic Acid, Linolenic Acid, Tocopherol, DMDM Hydantoin, Chlorohexidine Digluconate, Citric Acid, Zinc Sulfate, Tetrasodium EDTA, Red 4, Yellow 6

* Encountered in household settings

** Antibacterial Liquid Hand Wash

REFILL ONLY WITH DIAL COMPLETE ® TOTAL CLEAN FORMULA.

Questions? 1-800-258-DIAL

www.dialcomplete.com

©2014 & Distributed by THE DIAL CORPORATION
a Henkel COMPANY SCOTTSDALE, AZ 85255

Made in USA

The distinctive design and elements of this package are propriatary and
owned by The dial Corporation, A Henkel Company

Patent Pending

DOSAGE AND ADMINISTRATION

Topical Liquid

INDICATIONS AND USAGE

For handwashing to decrease bacteria on skin

PACKAGE LABEL

Kills 99.99% of Germs*

New Active!
TOTAL CLEAN FORMULA

Refill ONLY with Dial Complete® Total Clean Formula

Dial Complete® Foaming antibacterial Hand Wash

Gentle on skin

Omega Moisture with Sea Berries

7.5 FL OZ (221 mL)